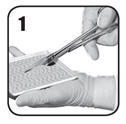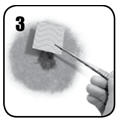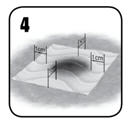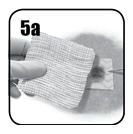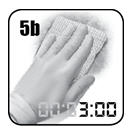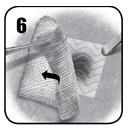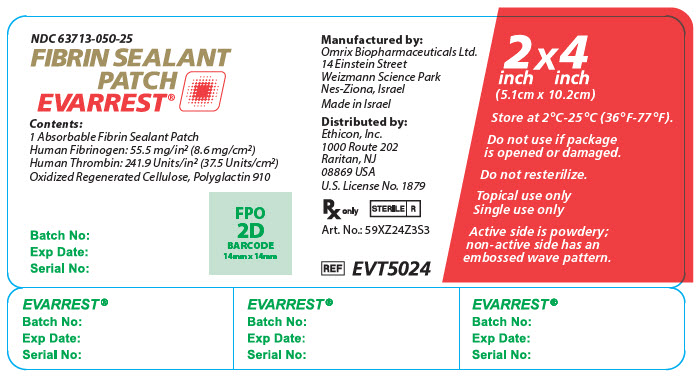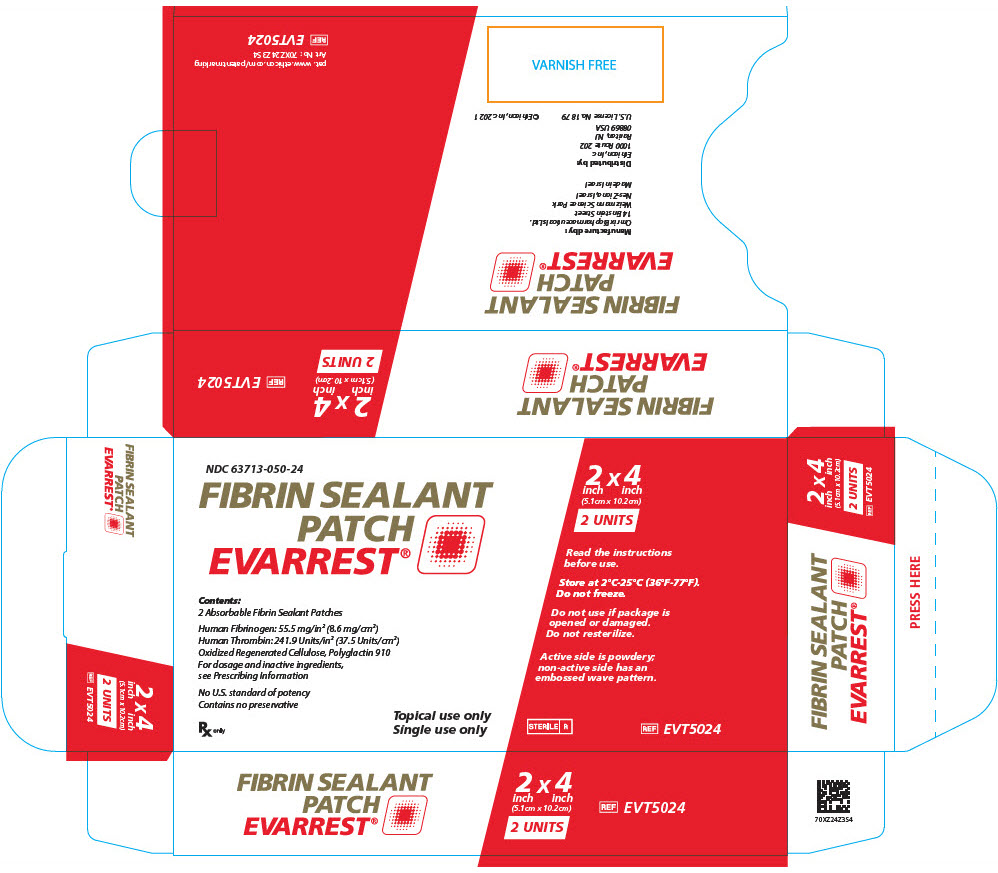 DRUG LABEL: EVARREST
NDC: 63713-050 | Form: PATCH
Manufacturer: Ethicon, Inc.
Category: other | Type: PLASMA DERIVATIVE
Date: 20250210

ACTIVE INGREDIENTS: FIBRINOGEN HUMAN 8.6 mg/1 cm2; HUMAN THROMBIN 37.5 [iU]/1 cm2
INACTIVE INGREDIENTS: ARGININE HYDROCHLORIDE; CALCIUM CHLORIDE; GLYCINE; ALBUMIN HUMAN; MANNITOL; SODIUM ACETATE; SODIUM CHLORIDE; SODIUM CITRATE, UNSPECIFIED FORM

HIGHLIGHTS OF PRESCRIBING INFORMATION

These highlights do not include all the information needed to use EVARREST®safely and effectively. See full prescribing information for EVARREST®.
EVARREST®Fibrin Sealant Patch
Absorbable Patch for Topical Use
Initial U.S. Approval: 2012

1 INDICATIONS AND USAGE

EVARREST® is a fibrin sealant patch indicated for use with manual compression as an adjunct to hemostasis in adult patients undergoing surgery, when control of bleeding by conventional surgical techniques (such as suture, ligature, and cautery) is ineffective or impractical.

(1)

Limitations for Use:

- Cannot be used in place of sutures or other forms of mechanical ligation in the treatment of major arterial or venous bleeding. (1)
- Not for use in children under one month of age (8.4)
- Laparoscopic and other minimally invasive surgeries where manual compression would be difficult to achieve.(1)

2 DOSAGE AND ADMINISTRATION

For topical use only.

- Determine the number of patches to be applied based upon the surface area and anatomic location of the bleeding tissue to be treated. (2)
- Keep the patch dry until use. (2.1)
- Place the powdery (active) side of the patch on the surface of tissue. (2.2)
- Apply immediate manual compression over the entire surface of the patch and maintain contact pressure for 3 minutes to control the bleeding. (2.2)

3 DOSAGE FORMS AND STRENGTHS

EVARREST®Fibrin Sealant Patch consists of human fibrinogen and human thrombin embedded in a flexible composite patch component. The active side is powdery, and the non-active side has an embossed wave pattern. (3)

Each 2 × 4 inch (5.1 × 10.2 cm) absorbable patch contains

- 55.5 mg per square inch (8.6 mg per square cm) human fibrinogen
- 241.9 Units per square inch (37.5 Units per square cm) human thrombin

4 CONTRAINDICATIONS

- Do not use to treat bleeding from large defects in arteries or veins. (4)
- Do not apply intravascularly. (4)
- Do not use in individuals known to have anaphylactic or severe systemic reaction to human blood products. (4)

5 WARNINGS AND PRECAUTIONS

- Thrombosis can occur if absorbed systemically. Apply topically to the bleeding site only. (5.1)
- Can cause hypersensitivity reactions including anaphylaxis. (5.2)
- Avoid application to contaminated areas of the body or in the presence of active infection. Infection can occur. (5.3)
- EVARREST®contains oxidized regenerated cellulose which adheres to bleeding surfaces. Inadvertent adhesions can occur. (5.4)
- Avoid use in, around, or in proximity to, foramina in bone or areas of bony confine where swelling may cause compression. (5.5)
- Use the least number of patches required to cover the entire bleeding area. (5.6)
- May carry a risk of transmitting infectious agents, e.g., viruses, the variant Creutzfeldt-Jakob disease (vCJD) agent and, theoretically, the Creutzfeldt-Jakob disease (CJD) agent. (5.7)

6 ADVERSE REACTIONS

The adverse reactions reported during clinical trials occurred in less than 1% of all cases and included deep venous thrombosis, pulmonary embolism, blood fibrinogen increase, anastomotic hemorrhage, post procedural and intra-abdominal hemorrhage, abdominal distension, anemia, gastrointestinal hemorrhage, thoracic cavity drainage, pleural effusion, abdominal abscess, ascites, localized intra-abdominal fluid collection, cardiac failure, operative hemorrhage, and ischemic bowel. (6)

To report SUSPECTED ADVERSE REACTIONS, contact ETHICON Customer Support Center at 1-877-384-4266 or FDA at 1-800-FDA-1088 or www.fda.gov/medwatch.

8 USE IN SPECIFIC POPULATIONS

Pediatric: Use in children under the age of one month may be unsafe or ineffective due to small size and limited ability to apply the patch as recommended. (8.4)

FULL PRESCRIBING INFORMATION

1 INDICATIONS AND USAGE

EVARREST®is a fibrin sealant patch indicated for use with manual compression as an adjunct to hemostasis in adult patients undergoing surgery, when control of bleeding by conventional surgical techniques (such as suture, ligature, and cautery) is ineffective or impractical.

Limitations for Use:

- Cannot safely or effectively be used in place of sutures or other forms of mechanical ligation in the treatment of major arterial or venous bleeding.
- Not for use in children under one month of age
- Laparoscopic and other minimally invasive surgeries where manual compression would be difficult to achieve.

2 DOSAGE AND ADMINISTRATION

For topical use only.

- Determine the number of patches to be applied based upon the surface area and anatomic location of the bleeding to be treated.
- Do not use more than eight 2 × 4 inch (5.1 × 10.2 cm) patches.
- Use in patients who have been previously exposed to EVARREST®has not been studied.

2.1 Preparation

- EVARREST®comes ready to use in sterile packages and must be handled using sterile technique in aseptic conditions. Discard damaged packages as resterilization is not possible.
- To open the product, remove the foil pouch from the carton, carefully peel open the foil pouch, avoiding contact with the inside of the foil or the white sterile tray containing EVARREST.
- Remove the white sterile tray from the pouch and place onto the sterile field.
- Hold the tray securely in the palm of the hand, ensuring that the side with the holes is facing upwards, and use the tabs on the side of the tray to remove the top of the tray with the other hand.
- The lower portion of the tray contains EVARREST with the active side facing downwards. The active side is powdery in appearance. The non-active side has an embossed wave pattern.
- Keep EVARREST dry after opening. The patch can remain in the sterile field to be available for use throughout the procedure. EVARREST does not stick to gloves, forceps, or surgical instruments.

2.2 Application

Apply topically to the bleeding site only.

1. Using sterile scissors, carefully cut the patch to the size and shape as necessary to fit and maintain contact with the bleeding area with an overlap of approximately 0.5 to 1 inch (1 to 2 cm). Keep the powdery white-to-yellow color active side of the patch facing down while in the tray.
2. Remove excess blood or fluid from the site of application to improve visibility. Do not use on non-visualized surfaces. Do not use to treat bleeding from defects in large arteries or veins where the injured vascular wall requires conventional surgical repair for maintenance of vessel patency.
3. Apply the active side of the patch to the bleeding area. Allow full contact with the tissue or prosthetic graft. The product is activated upon contact with fluid and then adheres, conforming to tissue with continuous manual compression.
4. Apply a sufficient number of patches to adequately cover the entire bleeding area, with an overlap of approximately 0.5 to 1 inch (1 to 2 cm). Use the least number of patches to cover the bleeding area [see Warnings and Precautions (5.6)] .
5. (a) Hold dry or moist laparotomy pads or surgical gauze over EVARREST®to achieve full contact with the bleeding surface.
  (b) To ensure hemostasis, immediately apply continuous manual compression over the entire surface of the patch (including the area of overlap) sufficient to stem all bleeding. Ensure even pressure distribution, full tissue apposition and avoid movement of the patch over the entire bleeding area. Maintain continuous manual compression for 3 minutes.
6. Gently remove laparotomy pads or surgical gauze from the application site without disrupting or dislodging EVARREST or the clot. If irrigation is necessary, use care not to dislodge the patch. Inspect the patch to ensure that it is in full contact with the treated area. If placement of the patch is unsatisfactory, remove the patch and use a new patch [see Dosage and Administration (2)] . Removal of the patch may disrupt the clot and result in re-bleeding.
7. Discard unused, opened patches at the end of the procedure.

2.3 Retreatment

- Retreatment may be required if there are folds, creases, or crimps in the patch. If not satisfied with the placement of the patch, or if bleeding still occurs during or after the specified duration of compression, remove the used patch and repeat the application procedure above with a new patch.
- If continued bleeding is due to insufficient coverage of the bleeding area, additional patches may be applied. Ensure that the edges overlap (by approximately 0.5 to 1 inch or 1 to 2 cm) with the existing patch.
- If continued bleeding is due to incomplete adherence to the tissue (where bleeding persists from under the dressing), remove the patch and use a new one.

3 DOSAGE FORMS AND STRENGTHS

EVARREST®Fibrin Sealant Patch consists of human fibrinogen and human thrombin embedded in a flexible composite patch component. The active side is white-to-yellow in color and powdery in appearance, and the non-active side has an embossed wave pattern.

Each 2 × 4 inch (5.1 × 10.2 cm) absorbable patch of EVARREST contains 55.5 mg per square inch (8.6 mg per square cm) of human fibrinogen and 241.9 Units [The Thrombin potency expressed in Units is determined using a clotting assay against an internal reference standard for potency that has been calibrated against the World Health Organization (WHO) Second International Standard for Thrombin, 01/580. Therefore, a Unit used herein is equivalent to an International Unit.] per square inch (37.5 Units per square cm) of human thrombin.

4 CONTRAINDICATIONS

Do not use EVARREST®for

- Bleeding from large defects in visible arteries or veins where the injured vascular wall requires conventional surgical repair and maintenance of vessel patency or where there would be persistent exposure of EVARREST to blood flow and/or pressure during absorption of the product.
- Intravascular application. This can result in life-threatening thromboembolic events.
- Individuals known to have anaphylactic or severe systemic reaction to human blood products.

5 WARNINGS AND PRECAUTIONS

5.1 Thrombosis

Thrombosis can occur if EVARREST®is absorbed systemically. Apply EVARREST topically to the bleeding site only.

5.2 Hypersensitivity Reactions

EVARREST®can cause hypersensitivity reactions, including anaphylactic reactions. Symptoms associated with allergic anaphylactic reactions include flush, urticaria, pruritus, nausea, drop in blood pressure, tachycardia or bradycardia, dyspnea, severe hypotension and anaphylactic shock.

5.3 Infection

Avoid application to contaminated or infected areas of the body, or in the presence of active infection. Infection can occur from application to an infected site.

5.4 Adhesions

EVARREST®contains oxidized regenerated cellulose which adheres to bleeding surfaces. Inadvertent adhesions can occur.

5.5 Compression

Avoid using EVARREST®in, around, or in proximity to, foramina in bone or areas of bony confine where swelling may cause nerve or blood vessel compression.

5.6 Dislodged Patch Material

Use the least number of patches possible during surgical procedures because portions of excess patch material can become dislodged and migrate to other areas of the body.

5.7 Transmissible Infectious Agents

Because the biological components of this product are made from human plasma, it may carry a risk of transmitting infectious agents, e.g., viruses, the variant Creutzfeldt-Jakob disease (vCJD) agent and, theoretically, the Creutzfeldt-Jakob disease (CJD) agent. The risk of transmitting viral agents has been minimized by screening plasma donors for prior exposure to certain viruses, by testing for the presence of certain current virus infections, and by inactivating and removing certain viruses during the manufacturing process [see Description (11)] . Despite these measures, such products still potentially can transmit disease. There is also the possibility that unknown infectious agents may be present in such products.

Any infection considered by a physician to possibly have been transmitted by this product should be reported by the physician or other healthcare provider to ETHICON Customer Support Center at 1-877-384-4266.

6 ADVERSE REACTIONS

All Adverse Reactions reported during the clinical trials occurred at a frequency of less than 1%. Most adverse reactions were reported as single events: intra-abdominal hemorrhage, abdominal distension, anemia, thoracic cavity drainage, pleural effusion, abdominal abscess, ascites, deep vein thrombosis, localized intra-abdominal fluid collection, operative hemorrhage, ischemic bowel and pulmonary embolism except blood fibrinogen increased (3 events, 0.8%) anastomotic hemorrhage (3 events, 0.8%) and post procedural hemorrhage (2 events, 0.5%).

6.1 Clinical Trials Experience

Because clinical trials are conducted under widely varying conditions, adverse reaction rates observed in clinical trials of a drug cannot be directly compared to rates of adverse reactions in clinical trials of another drug and may not reflect the rates observed in clinical practice.

EVARREST®was used to treat soft tissue bleeding during retroperitoneal, intra-abdominal, pelvic, or thoracic surgery, suture hole bleeding during cardiovascular surgery, and parenchymal bleeding during hepatic or renal surgery across all clinical trials involving 381 subjects treated with EVARREST and 272 control subjects. Of the enrolled subjects, 4.7% of EVARREST treated subjects (18 subjects out of 381) and 2.6% of control subjects (7 subjects out of 272) experienced one or more adverse reactions. Table 1 indicates the number of re-bleeding and thromboembolic events reported from each clinical trial.

Table 1. Re-bleeding and Thromboembolic Adverse Reactions Reported in Clinical Trials
System Organ Class | Preferred term | EVARREST All (n=381) | Relationship to Treatment | Control (n=272) | Relationship to Treatment
Abdominal, pelvic, retroperitoneal, and non-cardiac thoracic surgery
Injury, Poisoning and Procedural Complications | Operative Hemorrhage | 1 (0.3%) | Possibly related | 2 (0.7%) | Related and Possibly related
Respiratory, Thoracic and Mediastinal Disorders | Pulmonary Embolism | 1 (0.3%) | Possibly related | 0 (0.0%) | NA
Vascular Disorders | Deep Vein Thrombosis | 1 (0.3%) | Possibly related | 0 (0.0%) | NA
Liver Surgery
Gastrointestinal Disorders | Intra-Abdominal Hemorrhage | 1 (0.3%) | Possibly related | 0 (0.0%) | NA
Injury, Poisoning and Procedural Complications | Post Procedural Hemorrhage | 1 (0.3%) | Possibly related | 0 (0.0%) | NA
Renal Surgery
Injury, Poisoning and Procedural Complications | Post Procedural Hemorrhage | 1 (0.3%) | Related | 0 (0.0%) | NA
Cardiovascular Surgery
Injury, Poisoning and Procedural Complications | Anastomotic Hemorrhage | 3 (0.8%) | 2 × Related; 1 × Possibly related | 1 (0.4%) | Possibly related
 | Post Procedural Hemorrhage | 0 (0.0%) | NA | 2 (0.7%) | Possibly related

A prospective, randomized, controlled single-center post-marketing safety study observing the clinical utility of EVARREST against Standard of Care (SoC) in soft tissue bleeding during intra-abdominal, retroperitoneal, pelvic and non-cardiac thoracic surgery was conducted. Standard of Care was manual compression (MC) with or without a topical absorbable hemostat (TAH) or any other adjunctive hemostasis technique that was deemed by the surgeon to be his/her standard of care. The incidence of thromboembolic events, the incidence of post-operative bleeding events specifically related to the target bleeding site and the incidence of increased blood fibrinogen levels were assessed and recorded up to the 30 days (+/- 14 days) follow-up period.

The post-marketing study enrolled 150 subjects and demographics were balanced across the treatment groups. In both groups, no adverse events were assessed as re-bleeding related to target bleeding site; events assessed as thromboembolic events were experienced by 2/75 subjects (2.7%) in the EVARREST group and 7 subjects (9.3%) in the SoC group. One (1/75) adverse reaction of deep vein thrombosis was reported in the EVARREST group. No significant differences were observed in the frequency of adverse reactions between treatment groups.

Immunogenicity was evaluated in soft tissue clinical studies by testing blood samples collected for antibodies to human thrombin and fibrinogen. Three subjects out of 145 (~2%) in the group treated with EVARREST showed an increase in the titer of anti-thrombin antibodies after treatment. Two subjects out of 145 (~1%) in the group treated with EVARREST showed a transient increase in fibrinogen antibody titers, with titer levels back at background levels 8 to 10 weeks after treatment. None of the patients in any treatment group had a significant change in antibody titer to thrombin or fibrinogen. The general antibody level in the treated population was not affected by treatment with EVARREST and resembled the normal levels in healthy subjects.

6.2 Post Marketing Safety Data

No new safety signals were identified from post-marketing experience. There were no reported adverse events that were confirmed to be related to EVARREST. Two cases of post-operative infection were reported when EVARREST was used off-label in a contaminated area. In another two cases, lack of expected efficacy in achieving intraoperative hemostasis was reported in coagulopathic patients: however, because these were spontaneous reports, correct application of the product could not be confirmed.

8 USE IN SPECIFIC POPULATIONS

8.1 Pregnancy

Risk Summary

In the U.S. general population, the estimated background risk of major birth defects and miscarriage in clinically recognized pregnancies is 2-4% and 15-20%, respectively.

There are no data with EVARREST®use in pregnant women to inform a drug-associated risk. Animal reproduction studies have not been conducted with EVARREST. It is not known whether EVARREST can cause fetal harm when administered to a pregnant woman or can affect reproduction capacity. EVARREST should be applied to a pregnant woman only if clearly needed.

8.2 Lactation

Risk Summary

There is no information regarding the presence of any component of EVARREST®in human milk, the effect on the breastfed infant, or the effects on milk production. The developmental and health benefits of breastfeeding should be considered along with the mother's clinical need for EVARREST and any potential adverse effects on the breastfed infant from EVARREST or from the underlying maternal condition.

8.4 Pediatric Use

Safety and effectiveness in pediatric patients have not been established. Use of EVARREST®in children under the age of one month may be unsafe or ineffective due to small size and limited ability to apply the patch as recommended. Slow absorption and possibility of adhesions can further complicate use of EVARREST in the neonates.

8.5 Geriatric Use

Clinical trials included 181 subjects of 65 years of age or older who were treated with EVARREST®. No differences in safety or efficacy were observed between the elderly and younger patients.

11 DESCRIPTION

EVARREST®Fibrin Sealant Patch is a sterile, bio-absorbable combination product, comprised of two biological components (human plasma-derived fibrinogen and thrombin) embedded in a flexible composite patch component. The active side is white-to-yellow in color and powdery in appearance; the non-active side has an embossed wave pattern.

The patch component of EVARREST consists of an oxidized regenerated cellulose (ORC) layer underlying a layer of polyglactin 910 (PG910) non-woven fibers. The PG910 layer contains the embedded biological components. The patch component provides a large surface area for the biological components and imparts inherent mechanical integrity to the product. The flexibility of EVARREST accommodates the physiological movements of tissues and organs.

Each 2 × 4 inch (5.1 × 10.2 cm) EVARREST patch contains 55.5 mg per square inch (8.6 mg per square cm) of human fibrinogen and 241.9 Units per square inch (37.5 Units per square cm) of human thrombin. Additional inactive ingredients are: arginine hydrochloride, calcium chloride, glycine, human albumin, mannitol, sodium acetate, sodium chloride, and sodium citrate. EVARREST does not contain any preservative.

EVARREST is sterilized by electron-beam irradiation after completion of inner and outer packaging resulting in a sterile product in a sterile inner package.

Viral Clearance

The biological components of EVARREST®(human fibrinogen and human thrombin) are manufactured from pooled human plasma collected in FDA-licensed facilities in the United States. Human plasma is tested by FDA-licensed Nucleic Acid Tests (NAT) for hepatitis B virus (HBV), hepatitis C virus (HCV), and human immunodeficiency virus-1 (HIV-1). NAT testing for hepatitis A virus (HAV) and parvovirus B19 is also performed. In addition, human plasma is tested for the presence of hepatitis B surface antigen (HBsAg) and antibodies to hepatitis C virus (anti-HCV) and human immunodeficiency viruses types 1 and 2 (anti-HIV1/2).

The manufacturing procedure for human fibrinogen and human thrombin include processing steps designed to reduce the risk of viral transmission. In particular, the virus clearance steps in the manufacture of human fibrinogen include solvent/detergent (S/D) treatment and pasteurization. The virus clearance steps in the manufacture of human thrombin include S/D treatment and nanofiltration.

The virus clearance capacity of these procedures has been validated using viruses with a range of physico-chemical characteristics. These in vitrovalidation studies were conducted using samples from manufacturing intermediates spiked with virus suspensions of known titers followed by further processing under conditions equivalent to those in the respective manufacturing steps. The results of virus clearance validation studies are summarized in Table 2 and Table 3.

Table 2. Virus Reduction Factors for Human Fibrinogen
 | Reduction Factor (log10) of virus tested
 | [HIV-1: Human Immunodeficiency Virus Type 1 BVDV: Bovine Viral Diarrhea Virus PRV: Pseudorabies Virus] Enveloped Viruses |  |  | [EMCV: Encephalomyocarditis Virus HAV: Hepatitis A Virus CPV: Canine Parvovirus] Non-Enveloped Viruses
Manufacturing Step | HIV-1 | BVDV | PRV | EMCV | HAV | CPV
SD Treatment | > 4.42 | > 4.39 | > 3.96 | Not Tested | Not Tested | 0.0
Pasteurization | > 4.39 | > 5.46 | 6.04 | 3.69 | > 5.78 | 1.33
Cumulative Virus Reduction Factor | > 8.81 | > 9.85 | > 10.00 | 3.69 | > 5.78 | 1.33

Table 3. Virus Reduction Factors for Human Thrombin
 | Reduction Factor (log10) of virus tested
 | [HIV-1: Human Immunodeficiency Virus Type 1 SBV: Sindbis Virus BVDV: Bovine Viral Diarrhea Virus PRV: Pseudorabies Virus] Enveloped Viruses |  |  |  | [EMCV: Encephalomyocarditis Virus HAV: Hepatitis A Virus CPV: Canine Parvovirus] Non-Enveloped Viruses
Manufacturing Step | HIV-1 | SBV | BVDV | PRV | EMCV | HAV | CPV
SD Treatment | > 5.82 | > 5.31 | > 4.74 | > 4.25 | Not Tested | Not Tested | 0.0
Nanofiltration | > 4.36 | > 5.32 | Not Tested | > 5.47 | 6.37 | 6.95 | 5.85
Cumulative Virus Reduction Factor | > 10.18 | > 10.63 | > 4.74 | > 9.72 | 6.37 | 6.95 | 5.85

12 CLINICAL PHARMACOLOGY

12.1 Mechanism of Action

The mechanism of action of EVARREST®is based on the interaction between the biological components and the physiology of the fibrin clot formation. Upon contact with a bleeding wound surface, the biological components embedded in the patch component are hydrated, and the subsequent fibrinogen-thrombin reaction initiates the last step in the cascade of biochemical reactions - conversion of fibrinogen into fibrin monomers that further polymerize to form the fibrin clot.

Hemostasis is achieved when the formed fibrin clot integrates with the patch component and adheres to the wound surface thus also providing a physical barrier to bleeding.

13 NONCLINICAL TOXICOLOGY

13.1 Carcinogenesis, Mutagenesis, Impairment of Fertility

Long-term studies in animals to evaluate the carcinogenic potential of EVARREST®or studies to determine the effects of EVARREST on genotoxicity or fertility have not been performed. An assessment of the carcinogenic potential of EVARREST was completed to demonstrate minimal carcinogenic risk from product use.

13.2 Animal Toxicology and Pharmacology

The biological components of EVARREST are degraded by fibrinolysis and phagocytosis, similarly to endogenous fibrin. As resorption progresses, increased fibrinolytic activity is induced by plasmin, and decomposition of fibrin to fibrin degradation products is initiated. In swine and rodent models, topically applied EVARREST®was absorbed at approximately 8 weeks after application with less than 10% of the initial material remaining, which further degraded exponentially over time. In a rodent repeat-dosing model study, EVARREST was subcutaneously applied on Day 0 at twenty times the clinical dose at multiple surgical sites, or on Day 0 and 14 at ten times the clinical dose within multiple surgical sites. There was evidence of resorption at the site or sites of implantation after both single and repeated applications of EVARREST at study termination 90 days later. Repeat use of EVARREST in a rodent model was not associated with any increased local or systemic toxicological effects when used in multiple sites within the same procedure or when used in two procedures conducted 2-weeks apart at separate sites.

14 CLINICAL STUDIES

14.1 Abdominal, pelvic, retroperitoneal, and non-cardiac thoracic surgery

A prospective, randomized controlled trial including 141 subjects (median age: 62 years; range 26 to 89 years) was performed to compare the safety and hemostatic effectiveness of EVARREST®with that of oxidized regenerated cellulose (ORC), an absorbable hemostat, when used as an adjunct to control bleeding after primary methods to achieve hemostasis (e.g., suture, cautery, ligature) proved ineffective or impractical during open abdominal, pelvic, retroperitoneal, and non-cardiac thoracic surgery.

A total of 90 subjects were randomized in a 2:1 ratio (60 treated with EVARREST, 30 treated with ORC). An additional 51 subjects were enrolled and treated with EVARREST during a subsequent non-randomized phase. Of the total 141 enrolled subjects, 63.1% were male; 80.1% were White/Caucasian; 18.4% were Black; 0.7% were Asian; and 0.7% were Hispanic/Latino. Median body mass index was 27 kg/m^2(range: 17 to 53 kg/m^2). Demographic characteristics were balanced across treatment groups.

EVARREST demonstrated a statistically significant difference compared with ORC, 98.3% versus 53.3% (p < 0.0001) in the proportion of subjects achieving hemostatic success at 4 minutes after identification of the target bleeding site and randomization, with no re-bleeding requiring treatment during a subsequent 6-minute observation period and sustained hemostasis until fascial closure at the end of the surgery (Table 4).

Table 4. Subjects Achieving Hemostasis at 4 Minutes from Identification of the Target Bleeding Site and Randomization, with no Re-bleeding until Fascial Closure at the End of the Surgery
EVARREST® | ORC | p-value | Treatment Difference | 95% Confidence Interval
59/60 (98.3%) | 16/30 (53.3%) | <0.0001 | 45.0% | 27.9%, 62.5%

Efficacy data for the 51 non-randomized subjects treated with EVARREST were supportive of the above findings, with 50/51 subjects (98.0%) achieving hemostatic success at 4 minutes after randomization. No re-bleeding requiring treatment occurred during a subsequent 6-minute observation period.

14.2 Liver Surgery

Two prospective, randomized controlled trials including a total of 206 subjects were performed to compare the safety and hemostatic effectiveness of EVARREST®with that of Standard of Care (defined as manual compression with or without a topical absorbable hemostat) when used as an adjunct to control bleeding after primary methods to achieve hemostasis (e.g., suture, cautery, ligature) proved ineffective or impractical during liver surgery.

The first study included 104 subjects (median age: 65 years; range 31 to 82 years): 58.7% of the subjects were male; 95.2% were White/Caucasian; 1.9% were Asian; and 1% were Black. Median body mass index was 27kg/m^2(range: 15 to 43 kg/m^2). Demographic characteristics were balanced across treatment groups.

A total of 84 subjects were randomized in a 1:1 ratio (40 randomized to EVARREST, 44 to Standard of Care). An additional 20 subjects were enrolled and treated with EVARREST during a non-randomized phase. One subject should have been randomized to EVARREST but was treated with Standard of Care. This subject was analyzed in the EVARREST group for the Intent to Treat Set.

EVARREST demonstrated a statistically significant difference compared with Standard of Care (82.5% versus 29.5%; p < 0.0001) in the proportion of subjects achieving hemostatic success at 4 minutes after identification of the target bleeding site and randomization, with no re-bleeding requiring treatment any time prior to initiation of wound closure (Table 5). The treatment difference between EVARREST and Standard of Care was greater in subjects with bleeding from abnormal hepatic tissue (e.g., cirrhotic or steatotic) than in subjects with normal tissue bleeding (65.2% versus 48.8%, respectively).

Table 5. Subjects Achieving Hemostasis at 4 Minutes from Identification of the Target Bleeding Site and Randomization, with no Re-bleeding until Fascial Closure at the End of the Surgery
EVARREST® | Standard of Care | p-value | Treatment Difference | 95% Confidence Interval
33/40 (82.5%) | 13/44 (29.5%) | <0.0001 | 53.0% | 32.9%, 68.5%

Efficacy data for the 20 non-randomized subjects treated with EVARREST were supportive of the above findings, with 20/20 subjects (100.0%) achieving hemostatic success at 4 minutes after identification of the target bleeding site and randomization. No re-bleeding requiring treatment occurred any time prior to the initiation of wound closure.

The second study included 102 subjects (median age: 63 years; range 23 to 85 years) randomized in a 1:1 ratio (50 randomized to EVARREST, 52 to Standard of Care). Sixty-one percent of the subjects were male; 85.3% were White/Caucasian; 9.8% were Black; 2.9% were Asian; and 3% were Hispanic. Median body mass index was 27kg/m^2(range: 15 to 43 kg/m^2). Demographic characteristics were balanced across the treatment groups.

EVARREST demonstrated a statistically significant difference compared with Standard of Care (96% versus 46.2%; p < 0.0001) in the proportion of subjects achieving hemostatic success at 4 minutes after identification of the target bleeding site and randomization. No re-bleeding requiring treatment occurred at any time prior to initiation of wound closure (Table 6). The treatment difference between EVARREST and Standard of Care was shown to be greater in subjects undergoing non-anatomic resection than in subjects undergoing anatomic resection (58.1% versus 39.5%, respectively). Data from this study further support the efficacy of EVARREST as an adjunct to hemostasis in the control of bleeding in liver surgery.

Table 6. Subjects Achieving Hemostasis at 4 Minutes from Identification of the Target Bleeding Site and Randomization, with no Re-bleeding until Fascial Closure at the End of the Surgery
EVARREST® | Standard of Care | p-value | Treatment Difference | 95% Confidence Interval
48/50 (96.0%) | 24/52 (46.2%) | <0.0001 | 49.8% | 34.5%, 63.5%

14.3 Cardiovascular Surgery

Two prospective, randomized controlled trials enrolling a total of 198 subjects were performed to evaluate the safety and efficacy of EVARREST®as an adjunct to control of bleeding during cardiovascular surgery in subjects undergoing major aortic reconstruction using a synthetic graft (with the exception of ePTFE grafts) while on cardiopulmonary bypass and prior to heparin reversal. The target bleeding site was located on the tissue-graft or graft-graft anastomosis.

The first study included 42 subjects randomized 1:1:1 (13 randomized to EVARREST, 18 to TachoSil®, and 11 to Standard of Care). Median age was 56 years in the EVARREST cohort, 60 years in the TachoSil®Fibrin Sealant Patch (TachoSil®) cohort and 61 years in the Standard of Care cohort (range: 28-83 years). Standard of Care was defined as manual compression with or without a topical absorbable hemostat. The number of males exceeded the number of females (69.2% EVARREST, 83.3% TachoSil®and 81.8% Standard of Care) and most were White/Caucasian (69.2% EVARREST, 61.1% TachoSil®and 54.5% Standard of Care). Other demographic characteristics were balanced across treatment cohorts. The majority of subjects had a body mass index (BMI) categorized as "overweight" (BMI: 25 – <30 kg/m^2), "obese" (BMI: 30 – <40 kg/m^2) or "morbidly obese" (BMI ≥ 40 kg/m^2). These categories combined represented 61.6% of EVARREST subjects, 61.2% of TachoSil®subjects and 63.7% of Standard of Care subjects.

Table 7 shows a significant difference in hemostasis between EVARREST and TachoSil®(92.3% versus33.3%; 2.77; 95% CI 1.53, 5.74) and between EVARREST and Standard of Care (92.3% versus45.5%; 2.03; 95% CI 1.18, 4.39).

Table 7. Hemostasis at 3 Minutes with No Re-bleeding Until Initiation of Final Chest Wall Closure
Treatment Comparison | Hemostatic Efficacy Rates (%) |  | Risk Ratio (RR) | 95% CI [Using Koopman's method] for RR
EVARREST®to TachoSil® | 92.3% (12/13) | 33.3% (6/18) | 2.77 | (1.53, 5.74)
EVARREST®to SoC | 92.3% (12/13) | 45.5% (5/11) | 2.03 | (1.18, 4.39)

The second study included 156 subjects randomized 1:1 (76 randomized to EVARREST, 80 to TachoSil®). In both treatment cohorts, there were more males than females (75% EVARREST; 75% TachoSil®). Median age was 66 years in the EVARREST cohort and 64 years in the TachoSil®cohort (range: 24-83 years). The majority of subjects were White/Caucasian (82.9% EVARREST; 81. 3% TachoSil®). Median BMI in the EVARREST cohort was 27.1 kg/m^2(range 17.7 – 44.6 kg/m^2); 71.0% of subjects were categorized as "overweight" (BMI 25 – <30 kg/m^2), "obese" (BMI 30 – <40 kg/m^2) or "morbidly obese" (BMI ≥ 40 kg/m^2). Median BMI in the TachoSil®cohort was 27.9 kg/m^2(range 18.5 – 54.9 kg/m^2); 77.6% of subjects were categorized as "overweight", "obese" or "morbidly obese".

Table 8 shows that EVARREST was superior to TachoSil®in the proportion of subjects achieving hemostasis at the target anastomotic bleeding site at 3 minutes after treatment application and with no re-bleeding requiring treatment until chest wall closure (75.0% versus 45.0%; p = 0.0001). Data from this study support the efficacy of EVARREST as an adjunct to hemostasis in the control of bleeding in cardiovascular surgery.

Table 8. Subjects Achieving Hemostasis at 3 Minutes Following Treatment Application, With No Re-Bleeding Up Until Chest Wall Closure
EVARREST® | TachoSil® | p-value | Treatment Difference
57/76 (75.0%) | 36/80 (45.0%) | 0.0001 | 30.0%

16 HOW SUPPLIED/STORAGE AND HANDLING

EVARREST®is packaged in a polyester tray and lid assembly within an outer pouch composed of polyester laminated aluminum foil with an inner heat seal coating. The tray and lid assembly maintains product integrity during storage and transport. The aluminum foil pouch serves as a barrier to moisture and microbial contamination to maintain product sterility. Each aluminum foil pouch is contained in a labeled cardboard package.

Each individual package contains two 2 × 4 inch (5.1 × 10.2 cm) EVARREST patches (NDC 63713-050-25 per patch and NDC 63713-050-24 per package).

STORAGE AND HANDLING

- Use EVARREST before the expiration date indicated on the carton.
- Store unopened packages of EVARREST at 2 to 25°C. EVARREST does not require refrigeration. Do not freeze.
- Do not use if package is opened or damaged.
- Once opened, keep EVARREST dry to avoid activation of the biological components prior to use.

17 PATIENT COUNSELING INFORMATION

- Advise patients to consult their physician if they experience chest pain, shortness of breath, difficulty speaking or swallowing, leg tenderness or swelling, or other symptoms of thromboembolism.
- Inform patients that EVARREST®may carry a risk of transmitting infectious agents, e.g., viruses such as hepatitis A and parvovirus B19 and theoretically the CJD agent. Instruct patients to consult their physician if symptoms of B19 virus infection (fever, drowsiness, and chills, followed two weeks later by a rash and joint pain) or hepatitis A (several days to weeks of poor appetite, fatigue and low-grade fever followed by nausea, vomiting and abdominal pain, dark urine, yellowed complexion) appear.

Distributed by:
Ethicon Inc.
1000 Route 202
Raritan, NJ
08869 USA

Manufactured by:
Omrix Biopharmaceuticals Ltd.
14 Einstein Street
Weizmann Science Park
Nes-Ziona, Israel

US License No. 1879

© 2016 Ethicon, Inc.

Art. No. 80XZ24Z3S7

PRINCIPAL DISPLAY PANEL - 1 Patch Tray Label

NDC 63713-050-25

FIBRIN SEALANT
PATCH
EVARREST®

Contents:
1 Absorbable Fibrin Sealant Patch
Human Fibrinogen: 55.5 mg/in^2(8.6 mg/cm^2)
Human Thrombin: 241.9 Units/in^2(37.5 Units/cm^2)
Oxidized Regenerated Cellulose, Polyglactin 910

Batch No:
Exp Date:
Serial No:

FPO
2D
BARCODE
14mm x 14mm

Manufactured by:
Omrix Biopharmaceuticals Ltd.
14 Einstein Street
Weizmann Science Park
Nes-Ziona, Israel
Made in Israel

Distributed by:
Ethicon, Inc.
1000 Route 202
Raritan, NJ
08869 USA
U.S. License No. 1879

RXonly

STERILE R

Art. No.: 59XZ24Z3S3

REF EVT5024

2 x 4
inch inch
(5.1cm x 10.2cm)

Store at 2°C-25°C (36°F-77°F).

Do not use if package
is opened or damaged.

Do not resterilize.

Topical use only
Single use only

Active side is powdery;
non-active side has an
embossed wave pattern.

PRINCIPAL DISPLAY PANEL - 2 Patch Pouch Carton

NDC 63713-050-24

FIBRIN SEALANT
PATCH
EVARREST®

Contents:
2 Absorbable Fibrin Sealant Patches

Human Fibrinogen: 55.5 mg/in^2(8.6 mg/cm^2)
Human Thrombin: 241.9 Units/in^2(37.5 Units/cm^2)
Oxidized Regenerated Cellulose, Polyglactin 910
For dosage and inactive ingredients,
see Prescribing Information

No U.S. standard of potency
Contains no preservative

RXonly

Topical use only
Single use only

2 x 4
inch inch
(5.1cm x 10.2cm)

2 UNITS

Read the instructions
before use.

Store at 2°C-25°C (36°F-77°F).
Do not freeze.

Do not use if package is
opened or damaged.
Do not resterilize.

Active side is powdery;
non-active side has an
embossed wave pattern.

STERILE R

REF EVT5024